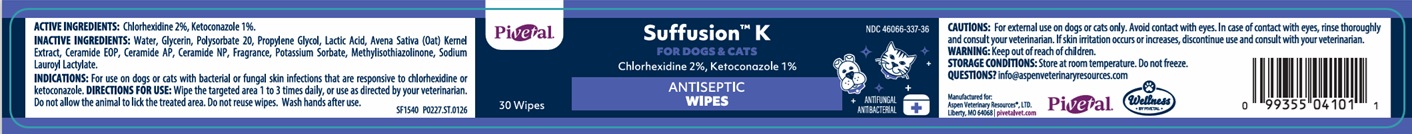 DRUG LABEL: Suffusion K ANTISEPTIC WIPES
NDC: 46066-337 | Form: CLOTH
Manufacturer: Aspen Veterinary Resources, LTD.
Category: animal | Type: OTC ANIMAL DRUG LABEL
Date: 20260212

ACTIVE INGREDIENTS: CHLORHEXIDINE 2 g/100 mL; KETOCONAZOLE 1 g/100 mL
INACTIVE INGREDIENTS: WATER; GLYCERIN; POLYSORBATE 20; PROPYLENE GLYCOL; LACTIC ACID, UNSPECIFIED FORM; OAT; CERAMIDE 9; CERAMIDE AP; CERAMIDE NP; POTASSIUM SORBATE; METHYLISOTHIAZOLINONE; SODIUM LAUROYL LACTYLATE

Pivetal® Suffusion™ K ANTISEPTIC WIPES

ACTIVE INGREDIENTS:

Chlorhexidine 2%, Ketoconazole 1%.

INACTIVE INGREDIENTS:

Water, Glycerin, Polysorbate 20, Propylene Glycol, Lactic Acid, Avena Sativa (Oat) Kernel Extract, Ceramide EOP, Ceramide AP, Ceramide NP, Fragrance, Potassium Sorbate, Methylisothiazolinone, Sodium Lauroyl Lactylate.

INDICATIONS:

For use on dogs or cats with bacterial or fungal skin infections that are responsive to chlorhexidine or ketoconazole.

DIRECTIONS FOR USE:

Wipe the targeted area 1 to 3 times daily, or use as directed by your veterinarian. Do not allow the animal to lick the treated area. Do not reuse wipes. Wash hands after use.

CAUTIONS:

For external use on dogs or cats only. Avoid contact with eyes. In case of contact with eyes, rinse thoroughly and consult your veterinarian. If skin irritation occurs or increases, discontinue use and consult with your veterinarian.

WARNING:

Keep out of reach of children.

STORAGE CONDITIONS:

Store at room temperature. Do not freeze.

QUESTIONS?

info@aspenveterinaryresources.com

FOR DOGS & CATS

ANTIFUNGAL
ANTIBACTERIAL

Manufactured for:
Aspen Veterinary Resources®, LTD.
Liberty, MO 64068 | pivetalvet.com